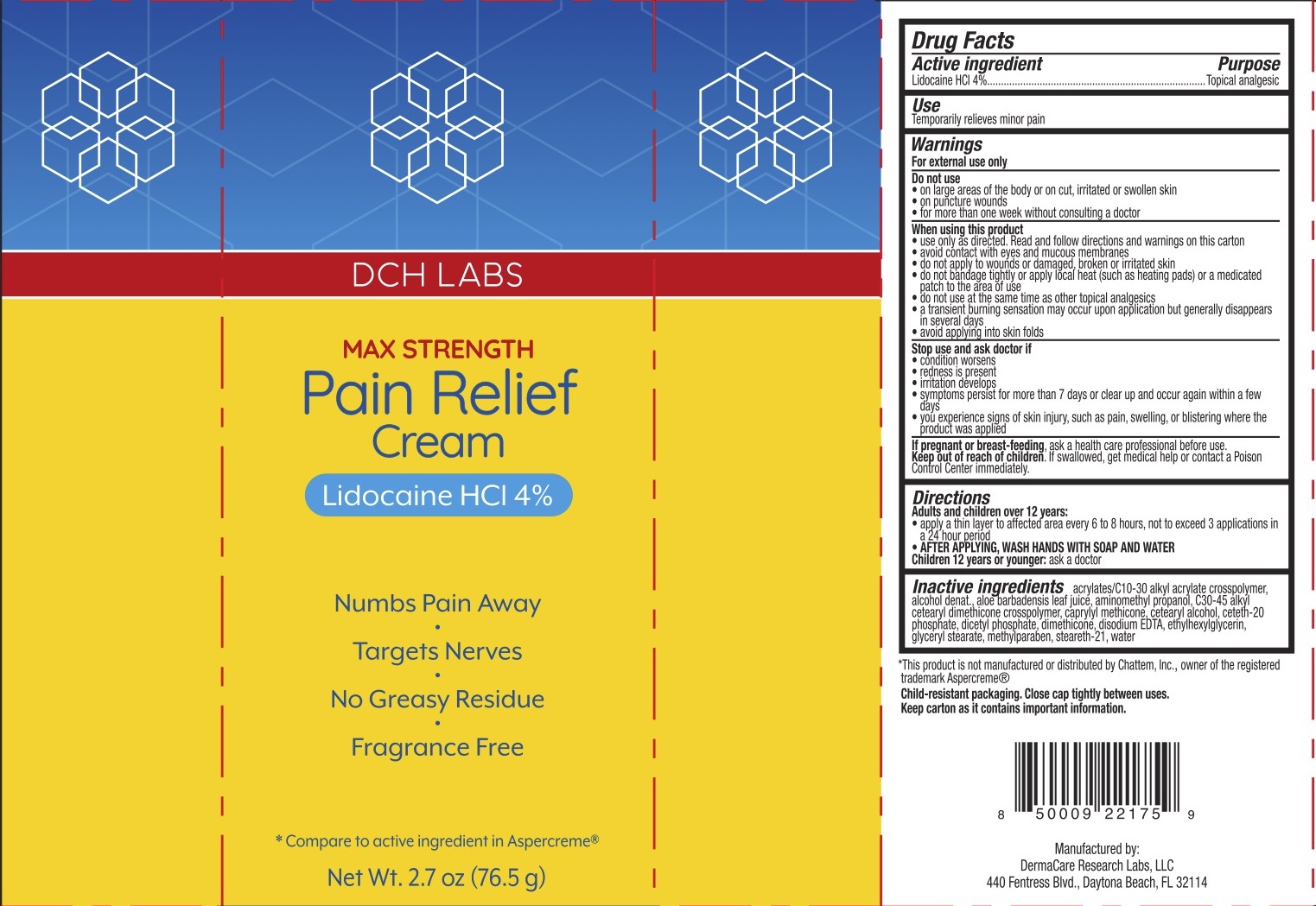 DRUG LABEL: DCH Pain Relief
NDC: 72839-361 | Form: CREAM
Manufacturer: Derma Care Research Labs, LLC
Category: otc | Type: HUMAN OTC DRUG LABEL
Date: 20241219

ACTIVE INGREDIENTS: LIDOCAINE HYDROCHLORIDE 4 g/100 g
INACTIVE INGREDIENTS: STEARETH-21; ETHYLHEXYLGLYCERIN; GLYCERYL MONOSTEARATE; CETETH-20 PHOSPHATE; CARBOMER COPOLYMER TYPE B (ALLYL PENTAERYTHRITOL CROSSLINKED); ALOE VERA LEAF; AMINOMETHYLPROPANOL; DIHEXADECYL PHOSPHATE; EDETATE DISODIUM; CAPRYLYL TRISILOXANE; METHYLPARABEN; CETOSTEARYL ALCOHOL; WATER; C30-45 ALKYL CETEARYL DIMETHICONE CROSSPOLYMER; DIMETHICONE 200; ALCOHOL

DCH Pain Relief Cream, Lidocaine HCl 4%

ACTIVE INGREDIENT

Lidocaine HCl 4%

PURPOSE

Topical Analgesic

DOSAGE AND ADMINISTRATION

Temporarily relieves minor pain.

WARNINGS

For external use only.

Do not use on large areas of the body or on cut, irritated, or swollen skin, on puncture wounds, for more than one week without consulting a doctor.

When using this product use only as directed. Read and follow directions on this carton, avoid contact with eyes and mucous membranes, do not apply to wounds or damaged, broken, or irritated skin, do not bandage tightly or apply local heat (such as heating pads) or a medicated patch to the area of use, do not use at the same time as other topical analgesics, a transient burning sensation may occur upon application but generally disappears in several days, avoid applying into skin folds.

Stop use and ask a doctor if the condition worsens, redness is present, irritation develops, symptoms persist for more than 7 days or clear up and occur again within a few days, you experience signs of skin injury, such as pain, swelling, or blistering where the product was applied.

KEEP OUT OF REACH OF CHILDREN

In case of accidental ingestion, seek professional assistance or contact a Poison Control Center immediately.

INDICATIONS AND USAGE

Adults and children over 12 years: apply a thin layer to the affected area every 6 to 8 hours, not to exceed 3 applications in a 24-hour period. AFTER APPLYING, WASH HANDS WITH SOAP AND WATER.

Children under 12 years or younger: ask a doctor.

INACTIVE INGREDIENT

Acrylates/C10-30 Alkyl Acrylate Crosspolymer, Alcohol Denat., Aloe Barbadensis Leaf Extract, Aminomethyl Propanol, C30-45 Alkyl Cetearyl Dimethicone Crosspolymer, Caprylyl Methicone, Cetearyl Alcohol, Ceteth-20 Phosphate, Dicetyl Phosphate, Dimethicone, Disodium EDTA, Ethylhexylglycerin, Glyceryl Stearate, Methylparaben, Steareth-21, Water.